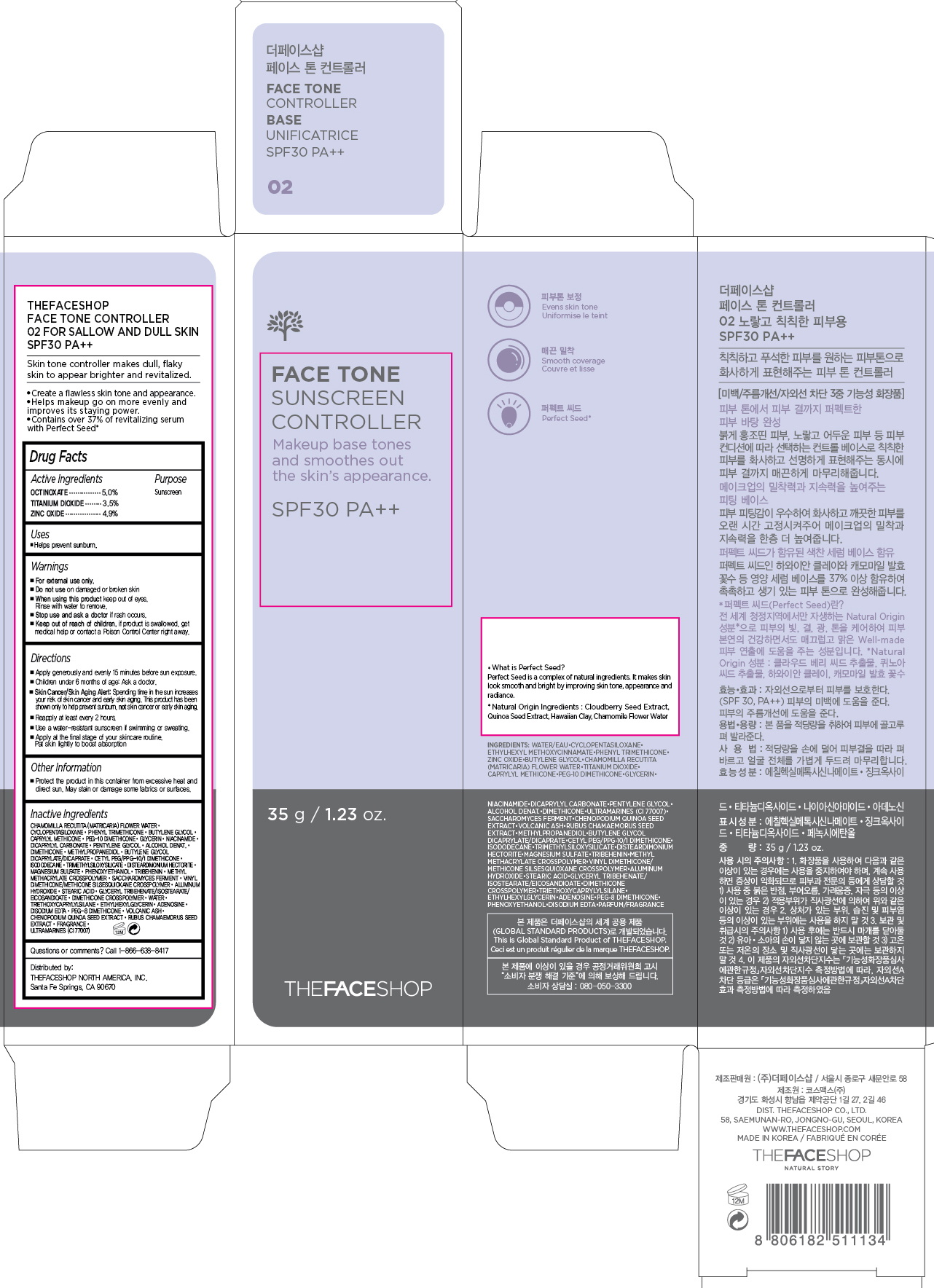 DRUG LABEL: FACE TONE
NDC: 51523-365 | Form: CREAM
Manufacturer: THEFACESHOP CO., LTD.
Category: otc | Type: HUMAN OTC DRUG LABEL
Date: 20150918

ACTIVE INGREDIENTS: OCTINOXATE 1.75 g/35 g; TITANIUM DIOXIDE 1.23 g/35 g; ZINC OXIDE 1.72 g/35 g
INACTIVE INGREDIENTS: WATER

FACE TONE Sunscreen Controller SPF30 PA++ 34200365

Active Ingredients

OCTINOXATE 5.0%

TITANIUM DIOXIDE 3.5 %

ZINC OXIDE 4.9%

Purpose

Sunscreen

Sunscreen

Sunscreen

Uses

Helps prevent sunburn

Warnings

For external use only.

Do not use on damaged or broken skin

When using this product keep out of eyes.

Rinse with water to remove.

Stop use and ask a doctor if rash occurs.

Keep out of reach of children. If product is swallowed, get

medical help or contact a Poison Control Center right away.

Directions

Apply generously and evenly 15 minutes before sun exposure.
Children under 6 months of age: Ask a doctor.
Skin Cancer/Skin Aging Alert: Spending time in the sun increases your risk of skin cancer and early skin aging. This product has been shown only to help prevent sunburn, not skin cancer or early skin aging.
Reapply at least every 2 hours.
Use a water-resistant sunscreen if swimming or sweating.

Apply at the final stage of your skincare routine. Pat skin lightly to boost absorption.

Other Information

Protect the product in this container from excessive heat and direct sun.

May stain or damage some fabrics or surfaces.

Inactive Ingredients

Chamomilla Recutita (Matricaria) Flower Water, Cyclopentasiloxane, Phenyl Trimethicone, Butylene Glycol, Caprylyl Methicone, PEG-10 Dimethicone, Glycerin, Niacinamide, Dicaprylyl Carbonate, Pentylene Glycol, Alcohol Denat., Dimethicone, Methylpropanediol, Butylene Glycol Dicaprylate/Dicaprate, Cetyl PEG/PPG-10/1 Dimethicone, Isododecane, Trimethylsiloxysilicate, Disteardimonium Hectorite, Magnesium Sulfate, Phenoxyethanol, Tribehenin, Methyl Methacrylate Crosspolymer, Saccharomyces Ferment, Vinyl Dimethicone/Methicone Silsesquioxane Crosspolymer, Aluminum Hydroxide, Stearic Acid, Glyceryl Tribehenate/Isostearate/Eicosandioate, Dimethicone Crosspolymer, Water, Triethoxycaprylylsilane, Ethylhexylglycerin, Adenosine, Disodium EDTA, PEG-8 Dimethicone, Volcanic Ash, Chenopodium Quinoa Seed Extract, Rubus Chamaemorus Seed Extract, Fragrance, Ultramarines (CI 77007)

Questions or comments? Call 1-866-638-8417

Distributed by:

THEFACESHOP NORTH AMERICA, INC.

Santa Fe Springs, CA 90670

PACKAGE LABEL

FACE TONE

SUNSCREEN CONTROLLER

02 FOR SALLOW AND DULL SKIN

SPF30 PA++

Skin tone controller makes dull, flaky

skin to appear brighter and revitalized.

•Create a flawless skin tone and appearance.

•Helps makeup go on more evenly and

improves its staying power.

•Contains over 37% of revitalizing serum

with Perfect Seed*